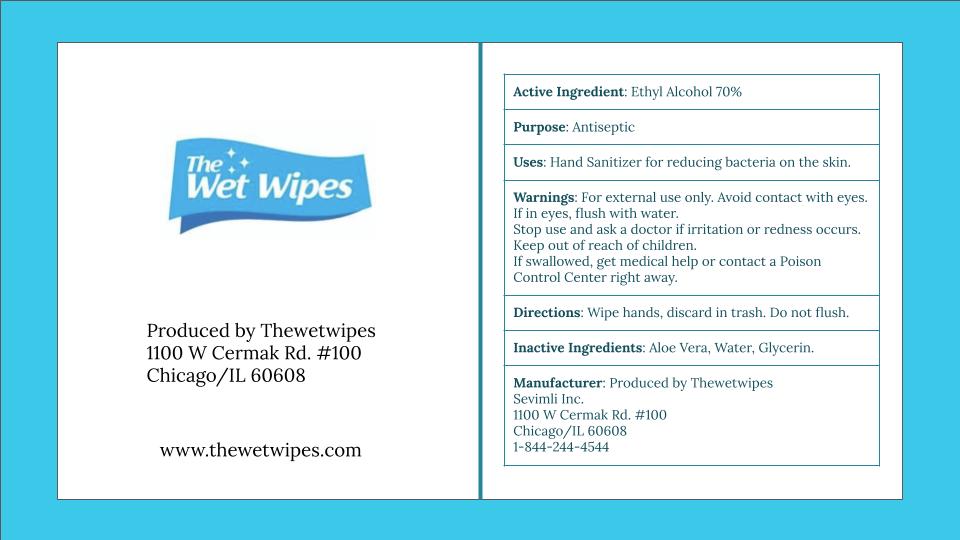 DRUG LABEL: The Wet Wipes
NDC: 81667-001 | Form: CLOTH
Manufacturer: Sevimli Inc.
Category: otc | Type: HUMAN OTC DRUG LABEL
Date: 20210203

ACTIVE INGREDIENTS: ALCOHOL 70 mg/100 mg
INACTIVE INGREDIENTS: GLYCERIN; ALOE VERA LEAF; WATER

Wet Wipes

Active Ingredient(s)

Ethyl Alcohol 70%

Purpose

Antiseptic

Use

Hand Sanitizer for reducing bacteria on the skin.

Warnings

For external use only.

WHEN USING

Avoid contact with eyes. If in eyes, flush with water.

Stop use and ask a doctor if irritation or redness occurs.

Keep out of reach of children. If swallowed, get medical help or contact a poison Control Center right away.

Directions

Wipe hands.

Inactive ingredients

glycerin, aloe vera, water

DISPOSAL AND WASTE HANDLING

Discard in trash. Do not flush.

Package Label - Principal Display Panel

The Wet Wipes

Produced by Thewetwipes

1100 w cermak rd. #100

chicago/IL 60608

www.thewetwipes.com